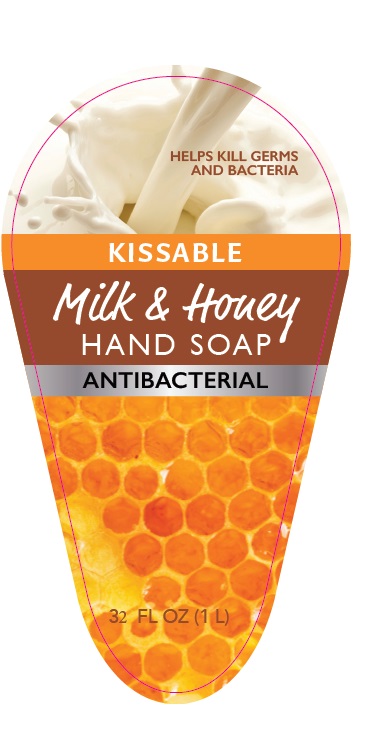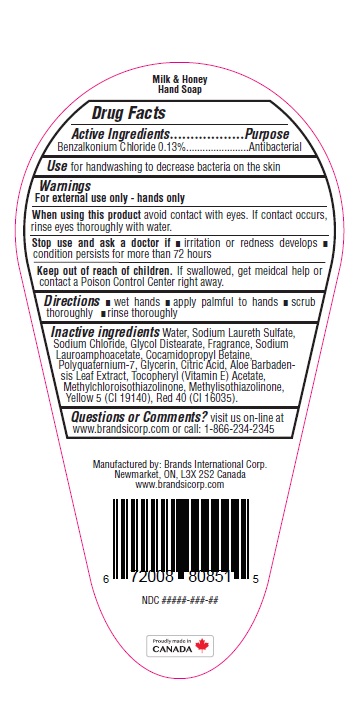 DRUG LABEL: Antibacterial

NDC: 50157-425 | Form: LIQUID
Manufacturer: Brands International Corporation
Category: otc | Type: HUMAN OTC DRUG LABEL
Date: 20210308

ACTIVE INGREDIENTS: BENZALKONIUM CHLORIDE 1.3 mg/1 mL
INACTIVE INGREDIENTS: WATER; SODIUM LAURETH SULFATE; COCAMIDOPROPYL BETAINE; SODIUM LAUROAMPHOACETATE; SODIUM CHLORIDE; GLYCERIN; GLYCOL DISTEARATE; POLYQUATERNIUM-7 (70/30 ACRYLAMIDE/DADMAC; 1600000 MW); METHYLCHLOROISOTHIAZOLINONE; METHYLISOTHIAZOLINONE; FD&C YELLOW NO. 5; CITRIC ACID MONOHYDRATE; ALOE VERA LEAF; .ALPHA.-TOCOPHEROL ACETATE; FD&C RED NO. 4

Kissable Milk & Honey - Hand Soap Antibacterial

ACTIVE INGREDIENT

Benzalkonium Chloride - 0.13%

Purpose: Antibacterial

DOSAGE AND ADMINISTRATION

Direction

- wet hands
- apply palmful to hands
- scrub thoroughly
- rinse

Warning

For external use only - Hands only

Stop use and ask a doctor

- if irritation or redness develops
- condition persists for more than 72 hours.

When using this product

- avoid contact with eyes.
- If contact occurs, rinse eye thoroughly with water

Keep out of reach of children

- If swallowed, get medical help or contact a Poison Control Center right away

INACTIVE INGREDIENT

Water, Sodium Laureth Sulfate, Cocamidopropyl Betaine, Sodium Chloride, Sodium Lauroamphoacetate , Polyquatemium-7, Citric Acid, Glycerin,

Aloe Barbadensis leaf Extract , Fragrance, Teocopheryl Acetate, Methylchloroisothiazolinone, Methylisothiazolinone, Yellow# 5 (Cl 19140), Red# 40(Cl 16035)

INDICATIONS AND USAGE

Uses for handwashing or decrease bacteria to the skin